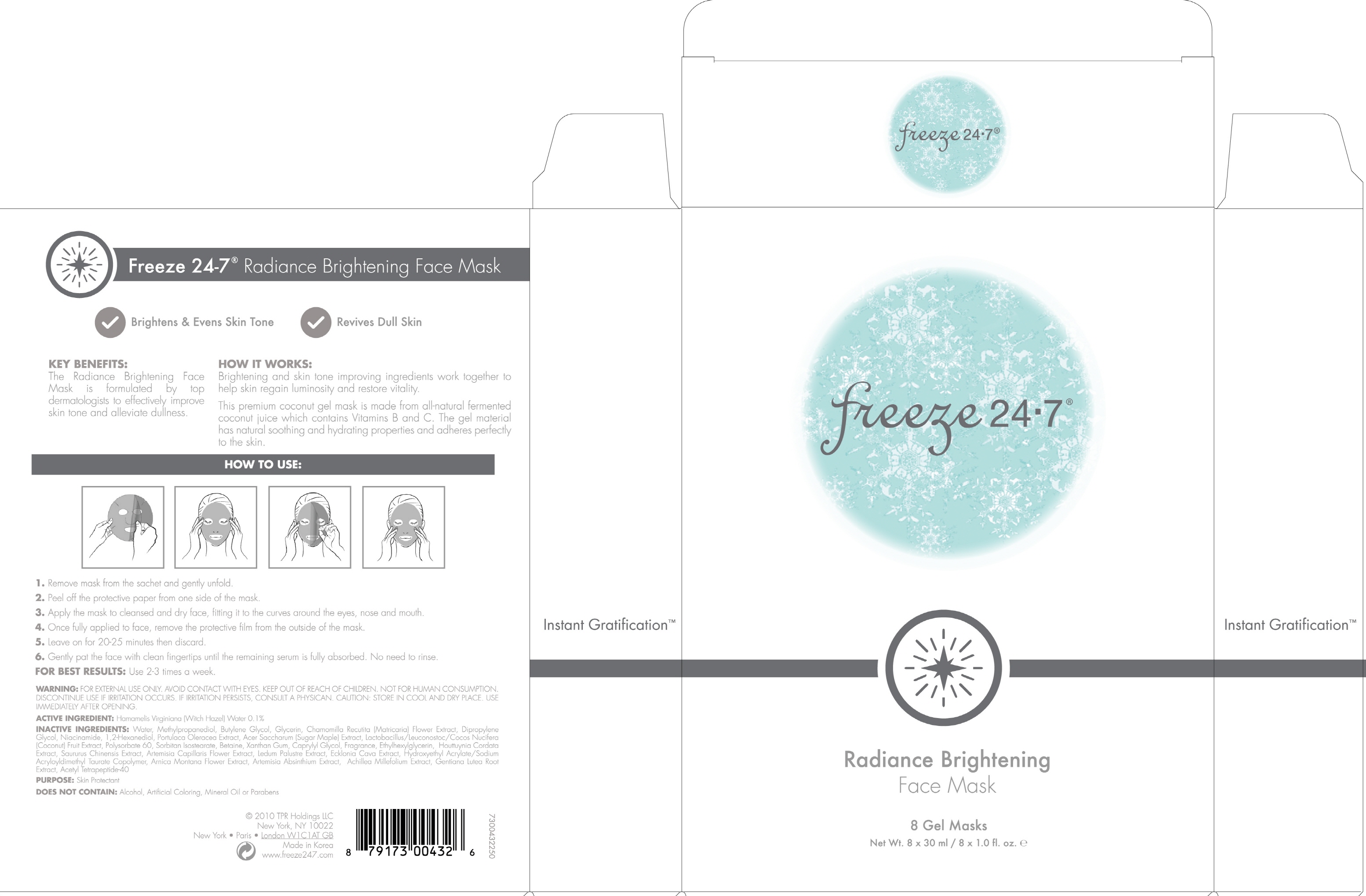 DRUG LABEL: FREEZE 24 7 RADIANCE BRIGHTENING FACE MASK
NDC: 70592-010 | Form: PATCH
Manufacturer: Summit C&T LLC
Category: otc | Type: HUMAN OTC DRUG LABEL
Date: 20160407

ACTIVE INGREDIENTS: Witch Hazel 0.03 g/30 mL
INACTIVE INGREDIENTS: Water; Methylpropanediol

ACTIVE INGREDIENT

Active Ingredient: Hamamelis Virginiana (Witch Hazel) Water 0.1%

INACTIVE INGREDIENT

Inactive Ingredients: Water, Methylpropanediol, Butylene Glycol, Glycerin, Chamomilla Recutita (Matricaria) Flower Extract, Dipropylene Glycol, Niacinamide, 1,2-Hexanediol, Portulaca Oleracea Extract, Acer Saccharum (Sugar Maple) Extract, Lactobacillus/Leuconostoc/Cocos Nucifera (Coconut) Fruit Extract, Polysorbate 60, Sorbitan Isostearate, Betaine, Xanthan Gum, Caprylyl Glycol, Fragrance, Ethylhexylglycerin, Houttuynia Cordata Extract, Saururus Chinensis Extract, Artemisia Capillaris Flower Extract, Ledum Palustre Extract, Ecklonia Cava Extract, Hydroxyethyl Acrylate/Sodium Acryloyldimethyl Taurate Copolymer, Arnica Montana Flower Extract, Artemisia Absinthium Extract, Achillea Millefolium Extract, Gentiana Lutea Root Extract, Acetyl Tetrapeptide-40

PURPOSE

Purpose: Skin protectant

WARNINGS

Warnings: For external use only. Avoid contact with eyes. Not for human consumption. Discontinue use if irritation occurs. If irritation persists, consult a physician. Use immediately after opening. Caution: Store in cool and dry place. Use Immediately after opening.

KEEP OUT OF REACH OF CHILDREN

INDICATIONS & USAGE

How to use: 1. Remove mask from the sachet and gently unfold. 2. Peel off the protective paper from one side of the mask. 3. Apply the mask to cleansed and dry face, fitting it to the curves around the eyes, nose and mouth. 4. Once fully applied to face, remove the protective film from the outside of the mask. 5. Leave on for 20-25 minutes then discard. 6. Gently pat the face with clean fingertips until the remaining serum is fully absorbed. No need to rinse.

DOSAGE & ADMINISTRATION

For Best Results: Suggested use is 2-3 times a week.